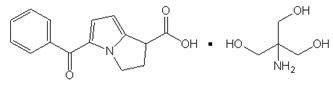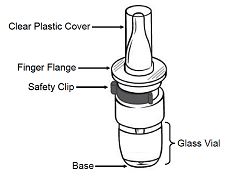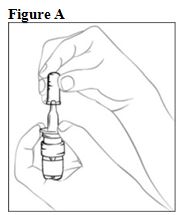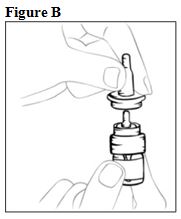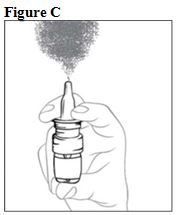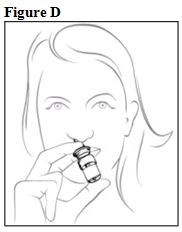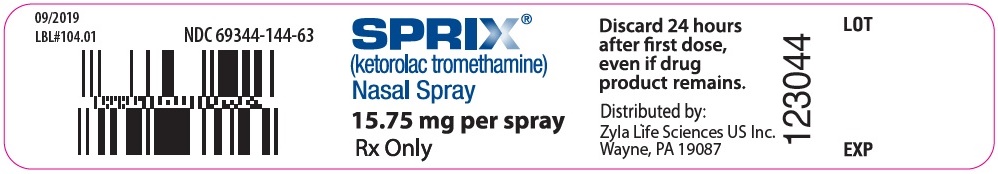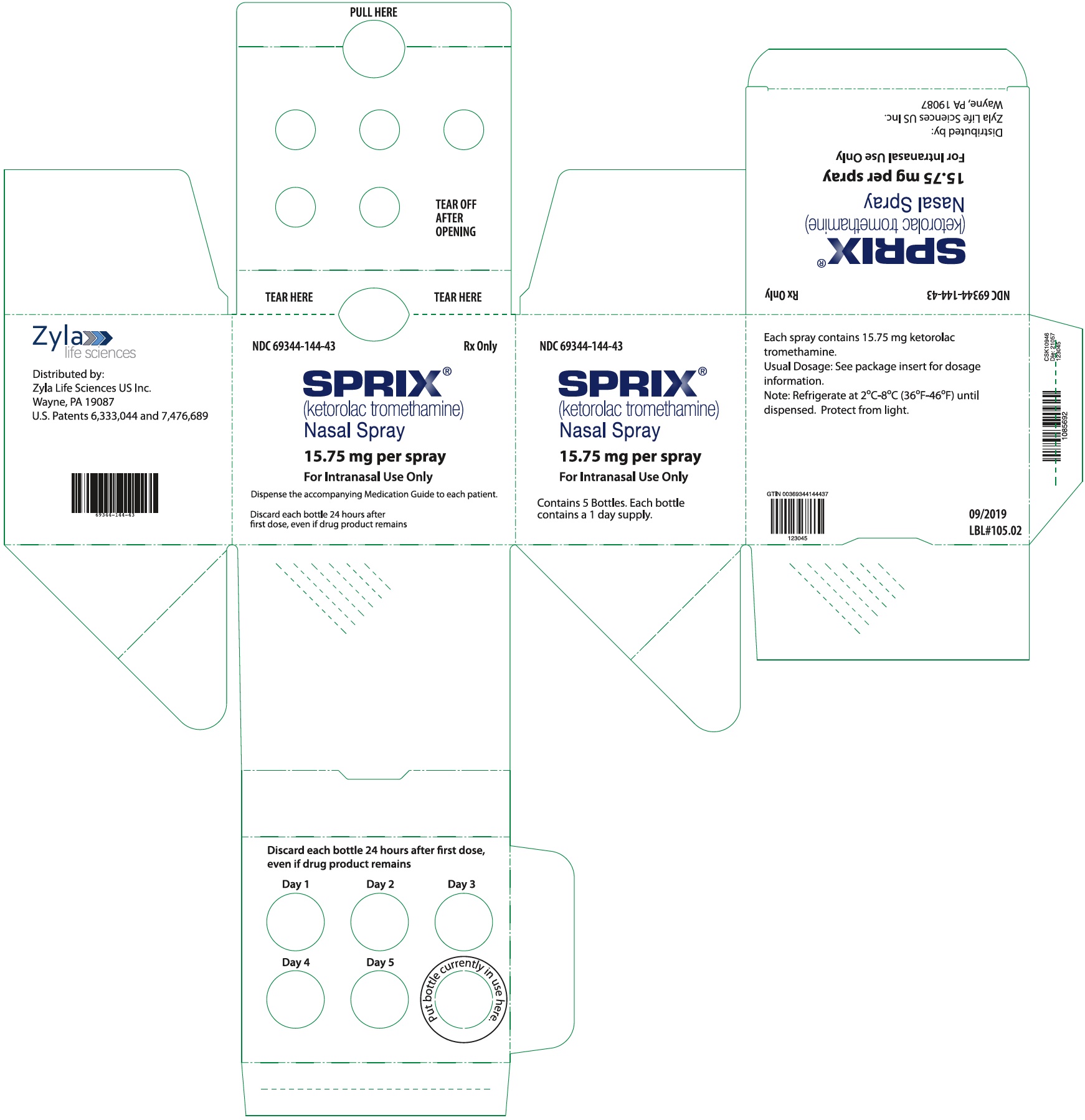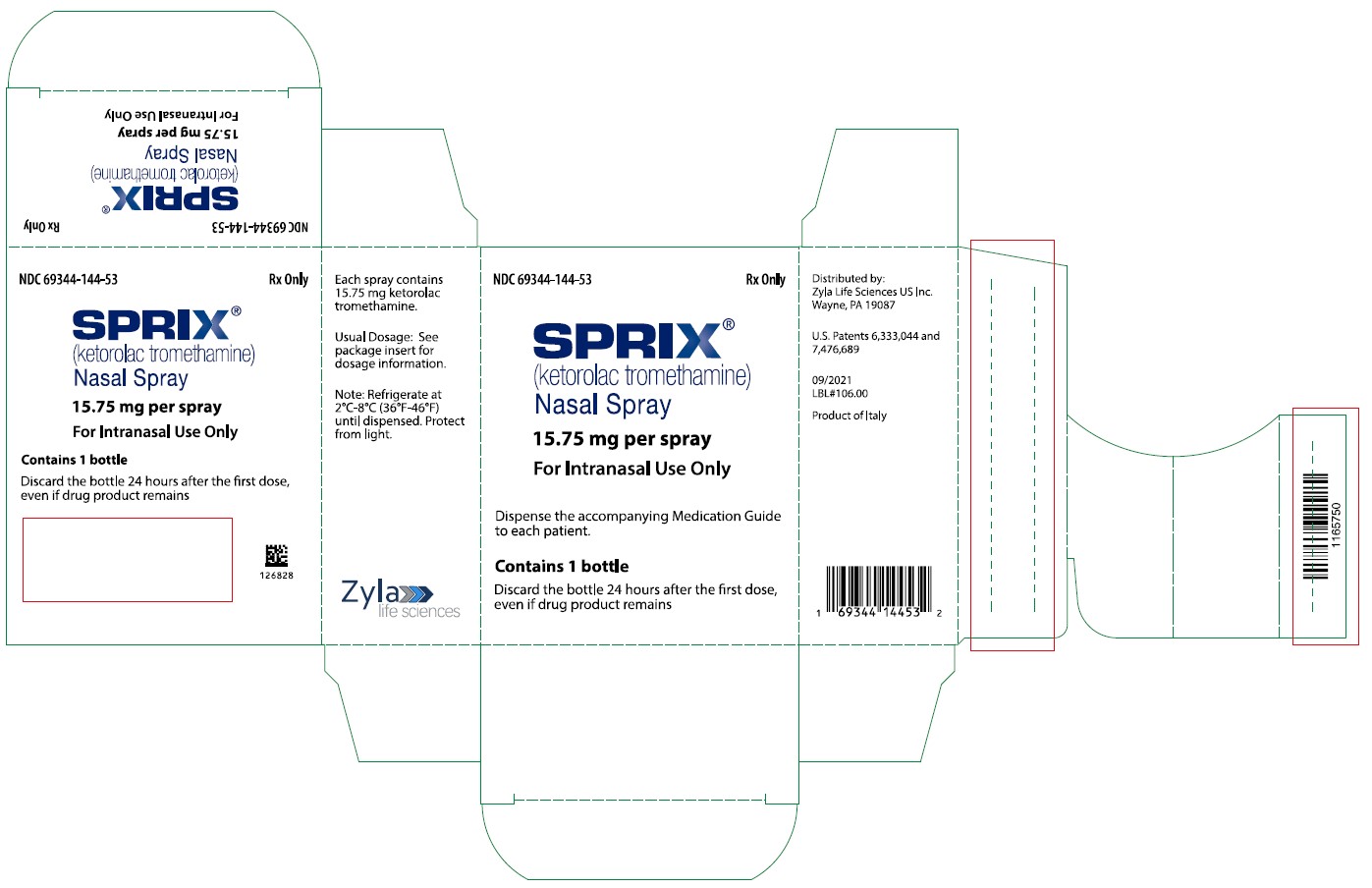 DRUG LABEL: Sprix
NDC: 69344-144 | Form: SPRAY, METERED
Manufacturer: Zyla Life Sciences US LLC
Category: prescription | Type: HUMAN PRESCRIPTION DRUG LABEL
Date: 20241205

ACTIVE INGREDIENTS: KETOROLAC TROMETHAMINE 15.75 mg/1 1
INACTIVE INGREDIENTS: EDETATE DISODIUM; POTASSIUM PHOSPHATE, MONOBASIC; SODIUM HYDROXIDE; WATER

HIGHLIGHTS OF PRESCRIBING INFORMATION

These highlights do not include all the information needed to use SPRIX® safely and effectively. See full prescribing information for SPRIX®.
SPRIX® (ketorolac tromethamine) Nasal Spray
Initial U.S. Approval: 1989

WARNING: RISK OF SERIOUS CARDIOVASCULAR AND GASTROINTESTINAL EVENTS

See full prescribing information for complete boxed warning.

- Nonsteroidal anti-inflammatory drugs (NSAIDS) cause an increased risk of serious cardiovascular thrombotic events, including myocardial infarction and stroke, which can be fatal. This risk may occur early in treatment and may increase with duration of use (5.1)
- SPRIX® is contraindicated in the setting of coronary artery bypass graft (CABG) surgery (4, 5.1)
- NSAIDS cause an increased risk of serious gastrointestinal (GI) adverse events including bleeding, ulceration, and perforation of the stomach or intestines, which can be fatal. These events can occur at any time during use and without warning symptoms. Elderly patients and patients with a prior history of peptic ulcer disease and/or GI bleeding are at greater risk for serious GI events (5.2)

RECENT MAJOR CHANGES

Warnings and Precautions (5.9) | 11/2024

1 INDICATIONS AND USAGE

SPRIX is a nonsteroidal anti-inflammatory drug indicated in adult patients for the short term (up to 5 days) management of moderate to moderately severe pain that requires analgesia at the opioid level. (1)

2 DOSAGE AND ADMINISTRATION

- Use the lowest effective dosage for shortest duration consistent with individual patient treatment goals. (2.1)
- SPRIX is not an inhaled product. For adult patients < 65 years of age: 31.5 mg (one 15.75 mg spray in each nostril) every 6 to 8 hours. The maximum daily dose is 126 mg. (2.2, 2.3)
- For patients ≥ 65 years of age, renally impaired patients, and patients less than 50 kg (110 lbs): 15.75 mg (one 15.75 mg spray in only one nostril) every 6 to 8 hours. The maximum daily dose is 63 mg. (2.4)
- SPRIX nasal spray should be discarded within 24 hours of taking the first dose, even if the bottle still contains some medication. (2.5)

3 DOSAGE FORMS AND STRENGTHS

SPRIX (ketorolac tromethamine) Nasal Spray: 15.75 mg of ketorolac tromethamine in each 100 μL spray. Each 1.7 g bottle contains 8 sprays. (3)

4 CONTRAINDICATIONS

- Known hypersensitivity to ketorolac or any components of the drug product (4)
- History of asthma, urticaria, or other allergic-type reactions after taking aspirin or other NSAIDs (4)
- In the setting of CABG surgery (4)
- Use in patients with active peptic ulcer disease or with recent GI bleeding or perforation (4)
- Use as a prophylactic analgesic before any major surgery (4)
- Use in patients with advanced renal disease or patients at risk for renal failure due to volume depletion (4)
- Use in patients with suspected or confirmed cerebrovascular bleeding, patients with hemorrhagic diathesis, incomplete hemostasis, and those at high risk of bleeding (4)
- Use in labor and delivery (4)

5 WARNINGS AND PRECAUTIONS

- Hepatotoxicity: Inform patients of warning signs and symptoms of hepatotoxicity. Discontinue if abnormal liver tests persist or worsen or if clinical signs and symptoms of liver disease develop. (5.3)
- Hypertension: Patients taking some antihypertensive medications may have impaired response to these therapies when taking NSAIDs. Monitor blood pressure. (5.4, 7)
- Heart Failure and Edema: Avoid use of SPRIX in patients with severe heart failure unless benefits are expected to outweigh risk of worsening heart failure. (5.5)
- Renal Toxicity: Monitor renal function in patients with renal or hepatic impairment, heart failure, dehydration, or hypovolemia. Avoid use of SPRIX in patients with advanced renal disease unless benefits are expected to outweigh risk of worsening renal function. (5.6)
- Anaphylactic Reactions: Seek emergency help if an anaphylactic reaction occurs. (5.7)
- Exacerbation of Asthma Related to Aspirin Sensitivity: SPRIX is contraindicated in patients with aspirin-sensitive asthma. Monitor patients with preexisting asthma (without aspirin sensitivity). (5.8)
- Serious Skin Reactions: Discontinue SPRIX at first appearance of skin rash or other signs of hypersensitivity. (5.9)
- Fetal Toxicity: Limit use of NSAIDs, including SPRIX, between about 20 to 30 weeks in pregnancy due to the risk of oligohydramnios/fetal renal dysfunction. Avoid use of NSAIDs in women at about 30 weeks gestation and later in pregnancy due to the risks of oligohydramnios/fetal dysfunction and premature closure of the fetal ductus arteriosus (5.10, 8.1)
- Drug Reaction with Eosinophilia and Systemic Symptoms (DRESS): Discontinue and evaluate clinically (5.11)
- Hematologic Toxicity: Monitor hemoglobin or hematocrit in patients with any signs or symptoms of anemia. Do not use SPRIX in patients for whom hemostasis is critical. (5.12, 7)
- Limitations of Use: SPRIX should not be used concomitantly with IM/IV or oral ketorolac, aspirin, or other NSAIDs. (5.16)

6 ADVERSE REACTIONS

Most common adverse reactions (incidence ≥2%) in patients treated with SPRIX and occurring at a rate at least twice that of placebo are nasal discomfort, rhinalgia, increased lacrimation, throat irritation, oliguria, rash, bradycardia, decreased urine output, increased ALT and/or AST, hypertension, and rhinitis. (6.1)

To report SUSPECTED ADVERSE REACTIONS, contact Zyla Life Sciences US Inc. at 1-800-518-1084 or FDA at 1-800-FDA-1088 or www.fda.gov/medwatch.

7 DRUG INTERACTIONS

- Drugs that Interfere with Hemostasis (e.g. warfarin, aspirin, SSRIs/SNRIs): Monitor patients for bleeding who are concomitantly taking SPRIX with drugs that interfere with hemostasis. Concomitant use of SPRIX and analgesic doses of aspirin is not generally recommended. (7)
- ACE inhibitors, Angiotensin Receptor Blockers (ARB), or Beta-Blockers: Concomitant use with SPRIX may diminish the antihypertensive effect of these drugs. Monitor blood pressure. (7)
- ACE Inhibitors and ARBs: Concomitant use with SPRIX in elderly, volume depleted, or those with renal impairment may result in deterioration of renal function. In such high risk patients, monitor for signs of worsening renal function. (7)
- Diuretics: NSAIDs can reduce natriuretic effect of furosemide and thiazide diuretics. Monitor patients to assure diuretic efficacy including antihypertensive effects. (7)
- Digoxin: Concomitant use with SPRIX can increase serum concentration and prolong half-life of digoxin. Monitor serum digoxin levels. (7)

8 USE IN SPECIFIC POPULATIONS

Infertility: NSAIDs are associated with reversible infertility. Consider withdrawal of SPRIX in women who have difficulties conceiving. (8.3)

FULL PRESCRIBING INFORMATION

WARNING: RISK OF SERIOUS CARDIOVASCULAR AND GASTROINTESTINAL EVENTS

Cardiovascular Thrombotic Events

- Nonsteroidal anti-inflammatory drugs (NSAIDs) cause an increased risk of serious cardiovascular thrombotic events, including myocardial infarction and stroke, which can be fatal. This risk may occur early in treatment and may increase with duration of use [see Warnings and Precautions (5.1)].
- SPRIX® is contraindicated in the setting of coronary artery bypass graft (CABG) surgery [see Contraindications (4) and Warnings and Precautions (5.1)].

Gastrointestinal Bleeding, Ulceration, and Perforation

- NSAIDs cause an increased risk of serious gastrointestinal (GI) adverse events including bleeding, ulceration, and perforation of the stomach or intestines, which can be fatal. These events can occur at any time during use and without warning symptoms. Elderly patients and patients with a prior history of peptic ulcer disease and/or GI bleeding are at greater risk for serious GI events [see Warnings and Precautions (5.2)].

1 INDICATIONS AND USAGE

SPRIX is indicated in adult patients for the short term (up to 5 days) management of moderate to moderately severe pain that requires analgesia at the opioid level.

Limitations of Use

- Sprix is not for use in pediatric patients less than 2 years of age.

2 DOSAGE AND ADMINISTRATION

2.1 General Dosing Instructions

Use the lowest effective dosage for the shortest duration consistent with individual patient treatment goals [see Warnings and Precautions (5)].

The total duration of use of SPRIX alone or sequentially with other formulations of ketorolac (IM/IV or oral) must not exceed 5 days because of the potential for increasing the frequency and severity of adverse reactions associated with the recommended doses [see Warnings and Precautions (5.15)].

Do not use SPRIX concomitantly with other formulations of ketorolac or other NSAIDs [see Warnings and Precautions (5.15)].

2.2 Administration

SPRIX is not an inhaled product. Do not inhale when administering this product.

Instruct patients to administer as follows:

1. First hold the finger flange with fingers, and remove the clear plastic cover with opposite hand; then remove the blue plastic safety clip. Keep the clear plastic cover; and throw away the blue plastic safety clip.

2. Before using the bottle for the FIRST time, activate the pump. To activate the pump, hold the bottle at arm’s length away from the body with index finger and middle finger resting on the top of the finger flange and thumb supporting the base.

Press down evenly and release the pump 5 times. Patient may not see a spray the first few times he/she presses down.

The bottle is now ready to use. There is no need to activate the pump again if more doses are used from the bottle.

3. It’s important to get the medication to the correct place in the nose so it will be most effective.

- Blow nose gently to clear nostrils.
- Sit up straight or stand. Tilt head slightly forward.
- Insert the tip of the container into your right nostril.
- Point the container away from the center of your nose.
- Hold your breath and spray once into your right nostril, pressing down evenly on both sides.
- Immediately after administration, resume breathing through mouth to reduce expelling the product. Also pinch the nose to help retain the spray if it starts to drip.

If only one spray per dose is prescribed, administration is complete; skip to Step 5 below.

4. If a dose of 2 sprays is prescribed, repeat the process in Step 3 for the left nostril. Again, be sure to point the spray away from the center of nose. Spray once into the left nostril.

5. Replace the clear plastic cover and place the bottle in a cool, dry location out of direct sunlight, such as inside a medication cabinet. Keep out of reach of children.

2.3 Adult Patients < 65 Years of Age

The recommended dose is 31.5 mg SPRIX (one 15.75 mg spray in each nostril) every 6 to 8 hours. The maximum daily dose is 126 mg (four doses).

2.4 Reduced Doses for Special Populations

For patients ≥ 65 years of age, renally impaired patients, and adult patients less than 50 kg (110 lbs), the recommended dose is 15.75 mg SPRIX (one 15.75 mg spray in only one nostril) every 6 to 8 hours. The maximum daily dose is 63 mg (four doses) [see Warnings and Precautions (5.2, 5.6)].

2.5 Discard Used SPRIX Bottle after 24 Hours

Do not use any single SPRIX bottle for more than one day as it will not deliver the intended dose after 24 hours. Therefore, the bottle must be discarded no more than 24 hours after taking the first dose, even if the bottle still contains some liquid.

3 DOSAGE FORMS AND STRENGTHS

SPRIX (ketorolac tromethamine) Nasal spray: 15.75 mg of ketorolac tromethamine in each 100 μL spray. Each 1.7 g bottle contains 8 sprays.

4 CONTRAINDICATIONS

SPRIX is contraindicated in the following patients:

- Known hypersensitivity (e.g., anaphylactic reactions and serious skin reactions) to ketorolac or any components of the drug product [see Warnings and Precautions (5.7, 5.9)]
- History of asthma, urticaria, or other allergic-type reactions after taking aspirin or other NSAIDs. Severe, sometimes fatal, anaphylactic reactions to NSAIDs have been reported in such patients [see Warnings and Precautions (5.7, 5.8)]
- In the setting of coronary artery bypass graft (CABG) surgery [see Warnings and Precautions (5.1)]
- Use in patients with active peptic ulcer disease and in patients with recent gastrointestinal bleeding or perforation [see Warnings and Precautions (5.2)]
- Use as a prophylactic analgesic before any major surgery [see Warnings and Precautions (5.11)]
- Use in patients with advanced renal disease or patients at risk for renal failure due to volume depletion [see Warnings and Precautions (5.6)]
- Use in labor and delivery. Through its prostaglandin synthesis inhibitory effect, ketorolac may adversely affect fetal circulation and inhibit uterine contractions, thus increasing the risk of uterine hemorrhage [see Use in Specific Populations (8.1)]
- Use in patients with suspected or confirmed cerebrovascular bleeding, hemorrhagic diathesis, incomplete hemostasis, or those for whom hemostasis is critical [see Warnings and Precautions (5.11), Drug Interactions (7)]
- Concomitant use with probenecid [see Drug Interactions (7)]
- Concomitant use with pentoxifylline [see Drug Interactions (7)]

5 WARNINGS AND PRECAUTIONS

5.1 Cardiovascular Thrombotic Events

Clinical trials of several COX-2 selective and nonselective NSAIDs of up to three years duration have shown an increased risk of serious cardiovascular (CV) thrombotic events, including myocardial infarction (MI) and stroke, which can be fatal. Based on available data, it is unclear that the risk for CV thrombotic events is similar for all NSAIDs. The relative increase in serious CV thrombotic events over baseline conferred by NSAID use appears to be similar in those with and without known CV disease or risk factors for CV disease. However, patients with known CV disease or risk factors had a higher absolute incidence of excess serious CV thrombotic events, due to their increased baseline rate. Some observational studies found that this increased risk of serious CV thrombotic events began as early as the first weeks of treatment. The increase in CV thrombotic risk has been observed most consistently at higher doses.

To minimize the potential risk for an adverse CV event in NSAID-treated patients, use the lowest effective dose for the shortest duration possible. Physicians and patients should remain alert for the development of such events, throughout the entire treatment course, even in the absence of previous CV symptoms. Patients should be informed about the symptoms of serious CV events and the steps to take if they occur.

There is no consistent evidence that concurrent use of aspirin mitigates the increased risk of serious CV thrombotic events associated with NSAID use. The concurrent use of aspirin and an NSAID, such as ketorolac, increases the risk of serious gastrointestinal (GI) events [see Warnings and Precautions (5.2)].

Status Post Coronary Artery Bypass Graft (CABG) Surgery

Two large, controlled clinical trials of a COX-2 selective NSAID for the treatment of pain in the first 10–14 days following CABG surgery found an increased incidence of myocardial infarction and stroke. NSAIDs are contraindicated in the setting of CABG [see Contraindications (4)].

Post-MI Patients

Observational studies conducted in the Danish National Registry have demonstrated that patients treated with NSAIDs in the post-MI period were at increased risk of reinfarction, CV-related death, and all-cause mortality beginning in the first week of treatment. In this same cohort, the incidence of death in the first year post-MI was 20 per 100 person years in NSAID-treated patients compared to 12 per 100 person years in non-NSAID exposed patients. Although the absolute rate of death declined somewhat after the first year post-MI, the increased relative risk of death in NSAID users persisted over at least the next four years of follow-up.

Avoid the use of SPRIX in patients with a recent MI unless the benefits are expected to outweigh the risk of recurrent CV thrombotic events. If SPRIX is used in patients with a recent MI, monitor patients for signs of cardiac ischemia.

5.2 Gastrointestinal Bleeding, Ulceration, and Perforation

SPRIX is contraindicated in patients with active peptic ulcers and/or GI bleeding and in patients with recent gastrointestinal bleeding or perforation [see Contraindications (4)].

NSAIDs, including ketorolac, cause serious gastrointestinal (GI) adverse events including inflammation, bleeding, ulceration, and perforation of the esophagus, stomach, small intestine, or large intestine, which can be fatal. These serious adverse events can occur at any time, with or without warning symptoms, in patients treated with NSAIDs. Only one in five patients who develop a serious upper GI adverse event on NSAID therapy is symptomatic. Upper GI ulcers, gross bleeding, or perforation caused by NSAIDs occurred in approximately 1% of patients treated for 3-6 months, and in about 2%-4% of patients treated for one year. However, even short-term NSAID therapy is not without risk.

Risk Factors for GI Bleeding, Ulceration, and Perforation

Patients with a prior history of peptic ulcer disease and/or GI bleeding who used NSAIDs had a greater than 10-fold increased risk for developing a GI bleed compared to patients without these risk factors. Other factors that increase the risk of GI bleeding in patients treated with NSAIDs include longer duration of NSAID therapy; concomitant use of oral corticosteroids, aspirin, anticoagulants, or selective serotonin reuptake inhibitors (SSRIs); smoking; use of alcohol; older age; and poor general health status. Most postmarketing reports of fatal GI events occurred in elderly or debilitated patients. Additionally, patients with advanced liver disease and/or coagulopathy are at increased risk for GI bleeding.

Strategies to Minimize the GI Risks in NSAID-treated patients:

- Use the lowest effective dosage for the shortest possible duration.
- Avoid administration of more than one NSAID at a time.
- Avoid use in patients at higher risk unless benefits are expected to outweigh the increased risk of bleeding. For such patients, consider alternate therapies other than NSAIDs. Do not use Sprix in those with active GI bleeding.
- Remain alert for signs and symptoms of GI ulceration and bleeding during NSAID therapy.
- If a serious GI adverse event is suspected, promptly initiate evaluation and treatment, and discontinue SPRIX until a serious GI adverse event is ruled out.
- In the setting of concomitant use of low-dose aspirin for cardiac prophylaxis, monitor patients more closely for evidence of GI bleeding [see Drug Interactions (7)].
- Use great care when giving SPRIX to patients with a history of inflammatory bowel disease (ulcerative colitis, Crohn’s disease) as their condition may be exacerbated.

5.3 Hepatotoxicity

Elevations of ALT or AST (three or more times the upper limit of normal [ULN]) have been reported in approximately 1% of NSAID-treated patients in clinical trials. In addition, rare, sometimes fatal, cases of severe hepatic injury, including fulminant hepatitis, liver necrosis, and hepatic failure have been reported.

Elevations of ALT or AST (less than three times ULN) may occur in up to 15% of patients treated with NSAIDs including ketorolac.

Inform patients of the warning signs and symptoms of hepatotoxicity (e.g., nausea, fatigue, lethargy, diarrhea, pruritus, jaundice, right upper quadrant tenderness, and "flu-like" symptoms). If clinical signs and symptoms consistent with liver disease develop, or if systemic manifestations occur (e.g., eosinophilia, rash, etc.), discontinue SPRIX immediately, and perform a clinical evaluation of the patient.

5.4 Hypertension

NSAIDs, including SPRIX, can lead to new onset of hypertension or worsening of preexisting hypertension, either of which may contribute to the increased incidence of CV events. Patients taking angiotensin converting enzyme (ACE) inhibitors, thiazide diuretics, or loop diuretics may have impaired response to these therapies when taking NSAIDs [see Drug Interactions (7)].

Monitor blood pressure (BP) during the initiation of NSAID treatment and throughout the course of therapy.

5.5 Heart Failure and Edema

The Coxib and traditional NSAID Trialists’ Collaboration meta-analysis of randomized controlled trials demonstrated an approximately two-fold increase in hospitalizations for heart failure in COX-2 selective-treated patients and nonselective NSAID-treated patients compared to placebo-treated patients. In a Danish National Registry study of patients with heart failure, NSAID use increased the risk of MI, hospitalization for heart failure, and death.

Additionally, fluid retention and edema have been observed in some patients treated with NSAIDs. Use of ketorolac may blunt the CV effects of several therapeutic agents used to treat these medical conditions (e.g., diuretics, ACE inhibitors, or angiotensin receptor blockers [ARBs]) [see Drug Interactions (7)].

Avoid the use of SPRIX in patients with severe heart failure unless the benefits are expected to outweigh the risk of worsening heart failure. If SPRIX is used in patients with severe heart failure, monitor patients for signs of worsening heart failure.

5.6 Renal Toxicity and Hyperkalemia

Ketorolac and its metabolites are eliminated primarily by the kidneys. Patients with reduced creatinine clearance will have diminished clearance of the drug [see Clinical Pharmacology (12.3)]. SPRIX is contraindicated in patients with advanced renal impairment [see Contraindications (4)].

Renal Toxicity

Long-term administration of NSAIDs has resulted in renal papillary necrosis and other renal injury. Renal toxicity has also been seen in patients in whom renal prostaglandins have a compensatory role in the maintenance of renal perfusion. In these patients, administration of an NSAID may cause a dose-dependent reduction in prostaglandin formation and, secondarily, in renal blood flow, which may precipitate overt renal decompensation. Patients at greatest risk of this reaction are those with impaired renal function, dehydration, hypovolemia, heart failure, liver dysfunction, those taking diuretics and ACE inhibitors or ARBs, and the elderly. Discontinuation of NSAID therapy is usually followed by recovery to the pretreatment state.

No information is available from controlled clinical studies regarding the use of SPRIX in patients with advanced renal disease. The renal effects of SPRIX may hasten the progression of renal dysfunction in patients with preexisting renal disease.

Correct volume status in dehydrated or hypovolemic patients prior to initiating SPRIX. Monitor renal function in patients with renal or hepatic impairment, heart failure, dehydration, or hypovolemia during use of SPRIX [see Drug Interactions (7)]. Avoid the use of SPRIX in patients with advanced renal disease unless the benefits are expected to outweigh the risk of worsening renal function. If SPRIX is used in patients with advanced renal disease, monitor patients for signs of worsening renal function.

Hyperkalemia

Increases in serum potassium concentration, including hyperkalemia, have been reported with use of NSAIDs, even in some patients without renal impairment. In patients with normal renal function, these effects have been attributed to a hyporeninemic-hypoaldosteronism state.

5.7 Anaphylactic Reactions

Ketorolac has been associated with anaphylactic reactions in patients with and without known hypersensitivity to ketorolac and in patients with aspirin-sensitive asthma [see Contraindications (4) and Warnings and Precautions (5.8)].

Seek emergency help if an anaphylactic reaction occurs.

5.8 Exacerbation of Asthma Related to Aspirin Sensitivity

A subpopulation of patients with asthma may have aspirin-sensitive asthma which may include chronic rhinosinusitis complicated by nasal polyps; severe, potentially fatal bronchospasm; and/or intolerance to aspirin and other NSAIDs. Because cross-reactivity between aspirin and other NSAIDs has been reported in such aspirin-sensitive patients, SPRIX is contraindicated in patients with this form of aspirin sensitivity [see Contraindications (4)]. When SPRIX is used in patients with preexisting asthma (without known aspirin sensitivity), monitor patients for changes in the signs and symptoms of asthma.

5.9 Serious Skin Reactions

NSAIDs, including ketorolac, can cause serious skin adverse reactions such as exfoliative dermatitis, Stevens-Johnson Syndrome (SJS), and toxic epidermal necrolysis (TEN), which can be fatal. NSAIDs can also cause fixed drug eruption (FDE). FDE may present as a more severe variant known as generalized bullous fixed drug eruption (GBFDE), which can be life-threatening. These serious events may occur without warning. Inform patients about the signs and symptoms of serious skin reactions, and to discontinue the use of SPRIX at the first appearance of skin rash or any other sign of hypersensitivity. SPRIX is contraindicated in patients with previous serious skin reactions to NSAIDs [see Contraindications (4)].

5.10 Drug Reaction with Eosinophilia and Systemic Symptoms (DRESS)

Drug Reaction with Eosinophilia and Systemic Symptoms (DRESS) has been reported in patients taking NSAIDs such as SPRIX. Some of these events have been fatal or life-threatening. DRESS typically, although not exclusively, presents with fever, rash, lymphadenopathy, and/or facial swelling. Other clinical manifestations may include hepatitis, nephritis, hematological abnormalities, myocarditis, or myositis. Sometimes symptoms of DRESS may resemble an acute viral infection. Eosinophilia is often present. Because this disorder is variable in its presentation, other organ systems not noted here may be involved. It is important to note that early manifestations of hypersensitivity, such as fever or lymphadenopathy, may be present even though rash is not evident. If such signs or symptoms are present, discontinue SPRIX and evaluate the patient immediately.

5.11 Fetal Toxicity

Premature Closure of Fetal Ductus Arteriosus

Avoid use of NSAIDs, including SPRIX, in pregnant women at about 30 weeks gestation and later. NSAIDs, including SPRIX, increase the risk of premature closure of the fetal ductus arteriosus at approximately this gestational age.

Oligohydramnios/Neonatal Renal Impairment

Use of NSAIDs, including SPRIX, at about 20 weeks gestation or later in pregnancy may cause fetal renal dysfunction leading to oligohydramnios and, in some cases, neonatal renal impairment. These adverse outcomes are seen, on average, after days to weeks of treatment, although oligohydramnios has been infrequently reported as soon as 48 hours after NSAID initiation.

Oligohydramnios is often, but not always, reversible with treatment discontinuation. Complications of prolonged oligohydramnios may, for example, include limb contractures and delayed lung maturation. In some postmarketing cases of impaired neonatal renal function, invasive procedures such as exchange transfusion or dialysis were required.

If NSAID treatment is necessary between about 20 weeks and 30 weeks gestation, limit SPRIX use to the lowest effective dose and shortest duration possible. Consider ultrasound monitoring of amniotic fluid if SPRIX treatment extends beyond 48 hours. Discontinue SPRIX if oligohydramnios occurs and follow up according to clinical practice [see Use in Specific Population (8.1)]

5.12 Hematologic Toxicity

Anemia has occurred in NSAID-treated patients. This may be due to occult or gross blood loss, fluid retention, or an incompletely described effect upon erythropoiesis. If a patient treated with SPRIX has any signs or symptoms of anemia, monitor hemoglobin or hematocrit. Do not use SPRIX in patients for whom hemostasis is critical [see Contraindications (4), Drug Interactions (7)].

NSAIDs, including SPRIX, may increase the risk of bleeding events. Co-morbid conditions such as coagulation disorders or concomitant use of warfarin, other anticoagulants, antiplatelet agents (e.g., aspirin), serotonin reuptake inhibitors (SSRIs) and serotonin norepinephrine reuptake inhibitors (SNRIs) may increase this risk. Monitor these patients for signs of bleeding [see Drug Interactions (7)].

The concurrent use of ketorolac and therapy that affects hemostasis, including prophylactic low dose heparin (2500 to 5000 units q12h), warfarin and dextrans, has not been studied extensively, but may also be associated with an increased risk of bleeding. Until data from such studies are available, carefully weigh the benefits against the risks and use such concomitant therapy in these patients only with extreme caution. Monitor patients receiving therapy that affects hemostasis closely.

In clinical trials, serious adverse events related to bleeding were more common in patients treated with SPRIX than placebo. In clinical trials and in postmarketing experience with ketorolac IV and IM dosing, postoperative hematomas and other signs of wound bleeding have been reported in association with peri-operative use. Therefore, use SPRIX with caution in the postoperative setting when hemostasis is critical.

5.13 Masking of Inflammation and Fever

The pharmacological activity of SPRIX in reducing inflammation, and possibly fever, may diminish the utility of diagnostic signs in detecting infections.

5.14 Laboratory Monitoring

Because serious GI bleeding, hepatotoxicity, and renal injury can occur without warning symptoms or signs, consider monitoring patients on long-term NSAID treatment with a CBC and a chemistry profile periodically [see Warnings and Precautions (5.2, 5.3, 5.6)].

5.15 Eye Exposure

Avoid contact of SPRIX with the eyes. If eye contact occurs, wash out the eye with water or saline, and consult a physician if irritation persists for more than an hour.

5.16 Limitations of Use

The total duration of use of SPRIX alone or sequentially with other forms of ketorolac is not to exceed 5 days. SPRIX must not be used concomitantly with other forms of ketorolac or other NSAIDs [see Dosage and Administration (2.1)].

6 ADVERSE REACTIONS

The following adverse reactions are discussed in greater detail in other sections of the labeling:

- Cardiovascular Thrombotic Events [see Warnings and Precautions (5.1)]
- GI Bleeding, Ulceration and Perforation [see Warnings and Precautions (5.2)]
- Hepatotoxicity [see Warnings and Precautions (5.3)]
- Hypertension [see Warnings and Precautions (5.4)]
- Heart Failure and Edema [see Warnings and Precautions (5.5)]
- Renal Toxicity and Hyperkalemia [see Warnings and Precautions (5.6)]
- Anaphylactic Reactions [see Warnings and Precautions (5.7)]
- Serious Skin Reactions [see Warnings and Precautions (5.9)]
- Hematologic Toxicity [see Warnings and Precautions (5.12)]

6.1 Clinical Trials Experience

Because clinical trials are conducted under widely varying conditions, adverse reaction rates observed in the clinical trials of a drug cannot be directly compared to rates in the clinical trials of another drug and may not reflect the rates observed in practice.

The data described below reflect exposure to SPRIX in patients enrolled in placebo-controlled efficacy studies of acute pain following major surgery. The studies enrolled 828 patients (183 men, 645 women) ranging from 18 years to over 75 years of age.

The patients in the postoperative pain studies had undergone major abdominal, orthopedic, gynecologic, or other surgery; 455 patients received SPRIX (31.5 mg) three or four times a day for up to 5 days, and 245 patients received placebo. Most patients were receiving concomitant opioids, primarily PCA morphine.

The most frequently reported adverse reactions were related to local symptoms, i.e., nasal discomfort or irritation. These reactions were generally mild and transient in nature.

The most common drug-related adverse events leading to premature discontinuation were nasal discomfort or nasal pain (rhinalgia).

Table 1: Post-Operative Patients with Adverse Reactions Observed at a Rate of 2% or More and at Least Twice the Incidence of the Placebo Group.
 | SPRIX (N = 455) | Placebo (N = 245)
Nasal discomfort | 15% | 2%
Rhinalgia | 13% | <1%
Lacrimation increased | 5% | 0%
Throat irritation | 4% | <1%
Oliguria | 3% | 1%
Rash | 3% | <1%
Bradycardia | 2% | <1%
Urine output decreased | 2% | <1%
ALT and/or AST increased | 2% | 1%
Hypertension | 2% | 1%
Rhinitis | 2% | <1%

In controlled clinical trials in major surgery, primarily knee and hip replacements and abdominal hysterectomies, seven patients (N=455, 1.5%) treated with SPRIX experienced serious adverse events of bleeding (4 patients) or hematoma (3 patients) at the operative site versus one patient (N=245, 0.4%) treated with placebo (hematoma). Six of the seven patients treated with SPRIX underwent a surgical procedure and/or blood transfusion and the placebo patient subsequently required a blood transfusion.

Adverse Reactions Reported in Clinical Trials with Other Dosage Forms of Ketorolac or Other NSAIDs

Adverse reaction rates increase with higher doses of ketorolac. It is necessary to remain alert for the severe complications of treatment with ketorolac, such as GI ulceration, bleeding, and perforation, postoperative bleeding, acute renal failure, anaphylactic and anaphylactoid reactions, and liver failure. These complications can be serious in certain patients for whom ketorolac is indicated, especially when the drug is used inappropriately.

In patients taking ketorolac or other NSAIDs in clinical trials, the most frequently reported adverse experiences in approximately 1% to 10% of patients are:

Gastrointestinal (GI) experiences including:
abdominal pain flatulence gross bleeding/perforation stomatitis | constipation/diarrhea GI fullness heartburn vomiting | dyspepsia GI ulcers (gastric/duodenal) nausea*
Other experiences:
abnormal renal function drowsiness headache* injection site pain rash | anemia edema hypertension pruritus tinnitus | dizziness elevated liver enzymes increased bleeding time purpura sweating
*Incidence greater than 10%

Additional adverse experiences reported occasionally (<1% in patients taking ketorolac or other NSAIDs in clinical trials) include:

Body as a Whole: fever, infection, sepsis

Cardiovascular System: congestive heart failure, palpitation, pallor, tachycardia, syncope

Digestive System: anorexia, dry mouth, eructation, esophagitis, excessive thirst, gastritis, glossitis, hematemesis, hepatitis, increased appetite, jaundice, melena, rectal bleeding

Hemic and Lymphatic: ecchymosis, eosinophilia, epistaxis, leukopenia, thrombocytopenia

Metabolic and Nutritional: weight change

Nervous System: abnormal dreams, abnormal thinking, anxiety, asthenia, confusion, depression, euphoria, extrapyramidal symptoms, hallucinations, hyperkinesis, inability to concentrate, insomnia, nervousness, paresthesia, somnolence, stupor, tremors, vertigo, malaise

Respiratory: asthma, dyspnea, pulmonary edema, rhinitis

Special Senses: abnormal taste, abnormal vision, blurred vision, hearing loss

Urogenital: cystitis, dysuria, hematuria, increased urinary frequency, interstitial nephritis, oliguria/polyuria, proteinuria, renal failure, urinary retention

6.2 Postmarketing Experience

The following adverse reactions have been identified during post approval use of ketorolac or other NSAIDs. Because these reactions are reported voluntarily from a population of uncertain size, it is not always possible to reliably estimate their frequency or establish a causal relationship to drug exposure.

Other observed reactions (reported from postmarketing experience in patients taking ketorolac or other NSAIDs) are:

Body as a Whole: angioedema, death, hypersensitivity reactions such as anaphylaxis, anaphylactoid reaction, laryngeal edema, tongue edema, myalgia

Cardiovascular: arrhythmia, bradycardia, chest pain, flushing, hypotension, myocardial infarction, vasculitis

Dermatologic: exfoliative dermatitis, erythema multiforme, Lyell's syndrome, bullous reactions including Stevens-Johnson syndrome, fixed drug eruption (FDE), and toxic epidermal necrolysis

Gastrointestinal: acute pancreatitis, liver failure, ulcerative stomatitis, exacerbation of inflammatory bowel disease (ulcerative colitis, Crohn’s disease)

Hemic and Lymphatic: agranulocytosis, aplastic anemia, hemolytic anemia, lymphadenopathy, pancytopenia, postoperative wound hemorrhage (rarely requiring blood transfusion)

Metabolic and Nutritional: hyperglycemia, hyperkalemia, hyponatremia

Nervous System: aseptic meningitis, convulsions, coma, psychosis

Respiratory: bronchospasm, respiratory depression, pneumonia

Special Senses: conjunctivitis

Urogenital: flank pain with or without hematuria and/or azotemia, hemolytic uremic syndrome

7 DRUG INTERACTIONS

See Table 2 for clinically significant drug interactions with ketorolac.

Table 2: Clinically Significant Drug Interactions with Ketorolac
Drugs that Interfere with Hemostasis
Clinical Impact: | - Ketorolac and anticoagulants such as warfarin have a synergistic effect on bleeding. The concomitant use of ketorolac and anticoagulants have an increased risk of serious bleeding compared to the use of either drug alone [see Clinical Pharmacology (12.3)]. - Serotonin release by platelets plays an important role in hemostasis. Case-control and cohort epidemiological studies showed that concomitant use of drugs that interfere with serotonin reuptake and an NSAID may potentiate the risk of bleeding more than an NSAID alone. - When ketorolac is administered concurrently with pentoxifylline, there is an increased risk of bleeding.
Intervention: | Monitor patients with concomitant use of SPRIX with anticoagulants (e.g., warfarin), antiplatelet agents (e.g., aspirin), selective serotonin reuptake inhibitors (SSRIs), and serotonin norepinephrine reuptake inhibitors (SNRIs) for signs of bleeding [see Warnings and Precautions (5.12)]. Concomitant use of SPRIX and pentoxifylline is contraindicated [see Contraindications (4) and Warnings and Precautions (5.12)].
Aspirin
Clinical Impact: | Controlled clinical studies showed that the concomitant use of NSAIDs and analgesic doses of aspirin does not produce any greater therapeutic effect than the use of NSAIDs alone. In a clinical study, the concomitant use of an NSAID and aspirin was associated with a significantly increased incidence of GI adverse reactions as compared to use of the NSAID alone [see Warnings and Precautions (5.2)].
Intervention: | Concomitant use of SPRIX and analgesic doses of aspirin is not generally recommended because of the increased risk of bleeding [see Warnings and Precautions (5.12)].
Intervention: | SPRIX is not a substitute for low dose aspirin for cardiovascular protection.
ACE Inhibitors, Angiotensin Receptor Blockers, and Beta-blockers
Clinical Impact: | - NSAIDs may diminish the antihypertensive effect of angiotensin converting enzyme (ACE) inhibitors, angiotensin receptor blockers (ARBs), or beta-blockers (including propranolol). - In patients who are elderly, volume-depleted (including those on diuretic therapy), or have renal impairment, co-administration of an NSAID with ACE inhibitors or ARBs may result in deterioration of renal function, including possible acute renal failure. These effects are usually reversible.
Intervention: | - During concomitant use of SPRIX and ACE-inhibitors, ARBs, or beta-blockers, monitor blood pressure to ensure that the desired blood pressure is obtained. - During concomitant use of SPRIX and ACE-inhibitors or ARBs in patients who are elderly, volume-depleted, or have impaired renal function, monitor for signs of worsening renal function [see Warnings and Precautions (5.6)]. - When these drugs are administered concomitantly, patients should be adequately hydrated. Assess renal function at the beginning of the concomitant treatment and periodically thereafter.
Diuretics
Clinical Impact: | Clinical studies, as well as post-marketing observations, showed that NSAIDs reduced the natriuretic effect of loop diuretics (e.g., furosemide) and thiazide diuretics in some patients. This effect has been attributed to the NSAID inhibition of renal prostaglandin synthesis
Intervention: | During concomitant use of SPRIX with diuretics, observe patients for signs of worsening renal function, in addition to assuring diuretic efficacy including antihypertensive effects [see Warnings and Precautions (5.6)].
Digoxin
Clinical Impact: | The concomitant use of ketorolac with digoxin has been reported to increase the serum concentration and prolong the half-life of digoxin.
Intervention: | During concomitant use of SPRIX and digoxin, monitor serum digoxin levels.
Lithium
Clinical Impact: | NSAIDs have produced elevations in plasma lithium levels and reductions in renal lithium clearance. The mean minimum lithium concentration increased 15%, and the renal clearance decreased by approximately 20%. This effect has been attributed to NSAID inhibition of renal prostaglandin synthesis.
Intervention: | During concomitant use of SPRIX and lithium, monitor patients for signs of lithium toxicity.
Methotrexate
Clinical Impact: | Concomitant use of NSAIDs and methotrexate may increase the risk for methotrexate toxicity (e.g., neutropenia, thrombocytopenia, renal dysfunction).
Intervention: | During concomitant use of SPRIX and methotrexate, monitor patients for methotrexate toxicity.
Cyclosporine
Clinical Impact: | Concomitant use of SPRIX and cyclosporine may increase cyclosporine’s nephrotoxicity.
Intervention: | During concomitant use of SPRIX and cyclosporine, monitor patients for signs of worsening renal function.
NSAIDs and Salicylates
Clinical Impact: | Concomitant use of ketorolac with other NSAIDs or salicylates (e.g., diflunisal, salsalate) increases the risk of GI toxicity, with little or no increase in efficacy [see Warnings and Precautions (5.2) and Clinical Pharmacology (12.3)].
Intervention: | The concomitant use of ketorolac with other NSAIDs or salicylates is not recommended.
Pemetrexed
Clinical Impact: | Concomitant use of SPRIX and pemetrexed may increase the risk of pemetrexed-associated myelosuppression, renal, and GI toxicity (see the pemetrexed prescribing information).
Intervention: | During concomitant use of SPRIX and pemetrexed, in patients with renal impairment whose creatinine clearance ranges from 45 to 79 mL/min, monitor for myelosuppression, renal and GI toxicity.; NSAIDs with short elimination half-lives (e.g., diclofenac, indomethacin) should be avoided for a period of two days before, the day of, and two days following administration of pemetrexed.; In the absence of data regarding potential interaction between pemetrexed and NSAIDs with longer half-lives (e.g., meloxicam, nabumetone), patients taking these NSAIDs should interrupt dosing for at least five days before, the day of, and two days following pemetrexed administration.
Probenecid
Clinical Impact: | Concomitant administration of oral ketorolac and probenecid results in increased half-life and systemic exposure. [see Clinical Pharmacology (12.3)].
Intervention: | Concomitant use of SPRIX and probenecid is contraindicated.
Antiepileptic Drugs
Clinical Impact: | Sporadic cases of seizures have been reported during concomitant use of ketorolac and antiepileptic drugs (phenytoin, carbamazepine).
Intervention: | During concomitant use of SPRIX and antiepileptic drugs, monitor patients for seizures.
Psychoactive Drugs
Clinical Impact: | Hallucinations have been reported when ketorolac was used in patients taking psychoactive drugs (fluoxetine, thiothixene, alprazolam).
Intervention: | During concomitant use of SPRIX and psychoactive drugs, monitor patients for hallucinations.
Nondepolarizing Muscle Relaxants
Clinical Impact: | In postmarketing experience there have been reports of a possible interaction between ketorolac and nondepolarizing muscle relaxants that resulted in apnea. The concurrent use of ketorolac with muscle relaxants has not been formally studied.
Intervention: | During concomitant use of SPRIX and nondepolarizing muscle relaxants, monitor patients for apnea.

8 USE IN SPECIFIC POPULATIONS

8.1 Pregnancy

Risk Summary
Use of NSAIDs, including SPRIX, can cause premature closure of the fetal ductus arteriosus and fetal renal
dysfunction leading to oligohydramnios and, in some cases, neonatal renal impairment. Because of these risks,
limit dose and duration of SPRIX use between about 20 and 30 weeks of gestation, and avoid SPRIX use at about
30 weeks of gestation and later in pregnancy (see Clinical Considerations, Data).

Premature Closure of Fetal Ductus Arteriosus

Use of NSAIDs, including SPRIX, at about 30 weeks gestation or later in pregnancy increases the risk of
premature closure of the fetal ductus arteriosus.

Oligohydramnios/Neonatal Renal Impairment

Use of NSAIDs at about 20 weeks gestation or later in pregnancy has been associated with cases of fetal
renal dysfunction leading to oligohydramnios, and in some cases, neonatal renal impairment.

Data from observational studies regarding other potential embryofetal risks of NSAID use in women in the first or
second trimesters of pregnancy are inconclusive. In animal reproduction studies in rabbits and rats tested at 0.6
and 1.5 times the human systemic exposure, respectively, at the recommended maximum IN dose of 31.5 mg four
times a day, there was no evidence of teratogenicity or other adverse developmental outcomes (see Data). Based
on animal data, prostaglandins have been shown to have an important role in endometrial vascular permeability,
blastocyst implantation, and decidualization. In animal studies, administration of prostaglandin synthesis
inhibitors such as ketorolac, resulted in increased pre- and post-implantation loss. Prostaglandins also have been
shown to have an important role in fetal kidney development. In published animal studies, prostaglandin synthesis
inhibitors have been reported to impair kidney development when administered at clinically relevant doses.

The estimated background risk of major birth defects and miscarriage for the indicated population(s) is unknown.
All pregnancies have a background risk of birth defect, loss, or other adverse outcomes. In the U.S. general
population, the estimated background risk of major birth defects and miscarriage in clinically recognized
pregnancies is 2% to 4% and 15% to 20%, respectively.

Clinical Considerations

Fetal/Neonatal Adverse Reactions

Premature Closure of Fetal Ductus Arteriosus:

Avoid use of NSAIDs in women at about 30 weeks gestation and later in pregnancy, because NSAIDs,
including SPRIX, can cause premature closure of the fetal ductus arteriosus (see Data).

Oligohydramnios/Neonatal Renal Impairment:

If an NSAID is necessary at about 20 weeks gestation or later in pregnancy, limit the use to the lowest
effective dose and shortest duration possible. If SPRIX treatment extends beyond 48 hours, consider
monitoring with ultrasound for oligohydramnios. If oligohydramnios occurs, discontinue SPRIX and
follow up according to clinical practice (see Data).

Data

Human Data

Premature Closure of Fetal Ductus Arteriosus:

Published literature reports that the use of NSAIDs at about 30 weeks of gestation and later in pregnancy
may cause premature closure of the fetal ductus arteriosus.

Oligohydramnios/Neonatal Renal Impairment:

Published studies and postmarketing reports describe maternal NSAID use at about 20 weeks gestation or
later in pregnancy associated with fetal renal dysfunction leading to oligohydramnios, and in some cases,
neonatal renal impairment. These adverse outcomes are seen, on average, after days to weeks of treatment,
although oligohydramnios has been infrequently reported as soon as 48 hours after NSAID initiation. In
many cases, but not all, the decrease in amniotic fluid was transient and reversible with cessation of the
drug. There have been a limited number of case reports of maternal NSAID use and neonatal renal
dysfunction without oligohydramnios, some of which were irreversible. Some cases of neonatal renal
dysfunction required treatment with invasive procedures, such as exchange transfusion or dialysis.

Methodological limitations of these postmarketing studies and reports include lack of a control group;
limited information regarding dose, duration, and timing of drug exposure; and concomitant use of other
medications. These limitations preclude establishing a reliable estimate of the risk of adverse fetal and
neonatal outcomes with maternal NSAID use. Because the published safety data on neonatal outcomes
involved mostly preterm infants, the generalizability of certain reported risks to the full-term infant
exposed to NSAIDs through maternal use is uncertain.

Animal Data

Reproduction studies have been performed during organogenesis using daily oral doses of ketorolac tromethamine at
3.6 mg/kg (0.6 times the human systemic exposure at the recommended maximum IN dose of 31.5 mg qid, based on
area-under-the-plasma-concentration curve [AUC]) in rabbits and at 10 mg/kg (1.5 times the human AUC) in rats.
These studies did not reveal evidence of teratogenicity or other adverse developmental outcomes. However, because
animal dosing was limited by maternal toxicity, these studies do not adequately assess ketorolac’s potential to cause
adverse developmental outcomes in humans.

8.2 Lactation

Risk Summary

Ketorolac is excreted in human milk. The developmental and health benefits of breastfeeding should be considered along with the mother’s clinical need for SPRIX and any potential adverse effects on the breastfed infant from the SPRIX or from the underlying maternal condition.

Clinical Considerations

Exercise caution when administering SPRIX to a nursing woman. Available information has not shown any specific adverse events in nursing infants; however, instruct patients to contact their infant’s health care provider if they note any adverse events.

Data

Limited data from one published study involving ten nursing mothers 2-6 days postpartum showed low levels of ketorolac in breast milk. Levels were undetectable (less than 5 ng/mL) in 4 of the patients. After a single administration of 10 mg ketorolac, the maximum milk concentration observed was 7.3 ng/mL, and the maximum milk to plasma ratio was 0.037. After 1 day of dosing (10 mg every 6 hours), the maximum milk concentration was 7.9 ng/mL, and the maximum milk-to-plasma ratio was 0.025. Assuming a daily intake of 400-1000 mL of human milk per day and a maternal body weight of 60 kg, the calculated maximum daily infant exposure was 0.00263 mg/kg/day, which is 0.4% of the maternal weight adjusted dose.

8.3 Females and Males of Reproductive Potential

Infertility

Females

Based on the mechanism of action, the use of prostaglandin-mediated NSAIDs, including SPRIX, may delay or prevent rupture of ovarian follicles, which has been associated with reversible infertility in some women. Published animal studies have shown that administration of prostaglandin synthesis inhibitors has the potential to disrupt prostaglandin-mediated follicular rupture required for ovulation. Small studies in women treated with NSAIDs have also shown a reversible delay in ovulation. Consider withdrawal of NSAIDs, including SPRIX, in women who have difficulties conceiving or who are undergoing investigation of infertility.

8.4 Pediatric Use

Sprix is not for use in pediatric patients less than 2 years of age. The safety and effectiveness of ketorolac in pediatric patients 17 years of age and younger have not been established.

8.5 Geriatric Use

Exercise caution when treating the elderly (65 years and older) with SPRIX. Elderly patients, compared to younger patients, are at greater risk for NSAID-associated serious cardiovascular, gastrointestinal, and/or renal adverse reactions. If the anticipated benefit for the elderly patient outweighs these potential risks, start dosing at the low end of the dosing range, and monitor patients for adverse effects [see Dosage and Administration (2.4), Warnings and Precautions (5.1, 5.2, 5.3, 5.6, 5.14), Clinical Pharmacology (12.3)]. After observing the response to initial therapy with SPRIX, adjust the dose and frequency to suit an individual patient’s needs.

Ketorolac and its metabolites are known to be substantially excreted by the kidneys, and the risk of adverse reactions to this drug may be greater in patients with impaired renal function. Because elderly patients are more likely to have decreased renal function, use caution in this patient population, and it may be useful to monitor renal function [see Clinical Pharmacology (12.3)].

10 OVERDOSAGE

Symptoms following acute NSAID overdosages have been typically limited to lethargy, drowsiness, nausea, vomiting, and epigastric pain, which have been generally reversible with supportive care. Gastrointestinal bleeding has occurred. Hypertension, acute renal failure, respiratory depression, and coma have occurred, but were rare [see Warnings and Precautions (5.1, 5.2, 5.4, 5.6)].

There has been no experience with overdosage of SPRIX. In controlled overdosage studies with IM ketorolac injection, daily doses of 360 mg given for five days (approximately 3 times the maximum daily dose of SPRIX) caused abdominal pain and peptic ulcers, which healed after discontinuation of dosing. Single overdoses of ketorolac tromethamine have been variously associated with abdominal pain, nausea, vomiting, hyperventilation, peptic ulcers and/or erosive gastritis, and renal dysfunction.

Manage patients with symptomatic and supportive care following an NSAID overdosage. There are no specific antidotes. Consider emesis and/or activated charcoal (60 to 100 grams in adults, 1 to 2 grams per kg of body weight in pediatric patients) and/or osmotic cathartic in symptomatic patients seen within four hours of ingestion or in patients with a large overdosage (5 to 10 times the recommended dosage). Forced diuresis, alkalinization of urine, hemodialysis, or hemoperfusion may not be useful due to high protein binding.

For additional information about overdosage treatment contact a poison control center (1-800-222-1222).

11 DESCRIPTION

SPRIX (ketorolac tromethamine) Nasal Spray is a member of the pyrrolo-pyrrole group of nonsteroidal anti-inflammatory drugs, available as a clear, colorless to yellow solution packaged in a glass vial with a snap on spray pump that delivers 15.75 mg ketorolac tromethamine per spray and is intended for intranasal administration. The chemical name is (±)-5-benzoyl-2,3-dihydro-1H-pyrrolizine-1-carboxylic acid, compound with 2-amino-2-(hydroxymethyl)-1,3-propanediol (1:1). The molecular weight is 376.41.

Its molecular formula is C19H24N2O6(C15H13NO3•C4H11NO3), and it has the following chemical structure.

Ketorolac tromethamine is highly water-soluble, allowing its formulation in an aqueous nasal spray product at pH 7.2.

The inactive ingredients in SPRIX include: edetate disodium (EDTA), monobasic potassium phosphate, sodium hydroxide, and water for injection.

12 CLINICAL PHARMACOLOGY

12.1 Mechanism of Action

Ketorolac has analgesic, anti-inflammatory, and antipyretic properties.

The mechanism of action of SPRIX, like that of other NSAIDs, is not completely understood but involves inhibition of cyclooxygenase (COX-1 and COX-2), an early component of the arachidonic acid cascade, resulting in the reduced synthesis of prostaglandins, thromboxanes, and prostacyclin.

Ketorolac is a potent inhibitor of prostaglandin synthesis in vitro. Ketorolac concentrations reached during therapy have produced in vivo effects. Prostaglandins sensitize afferent nerves and potentiate the action of bradykinin in inducing pain in animal models. Prostaglandins are mediators of inflammation. Because ketorolac is an inhibitor of prostaglandin synthesis, its mode of action may be due to a decrease of prostaglandins in peripheral tissues.

12.3 Pharmacokinetics

The half-lives of ketorolac by the IN and IM routes were similar. The bioavailability of ketorolac by the IN route of administration of a 31.5 mg dose was approximately 60% compared to IM administration. (See Table 3).

Table 3: Pharmacokinetic Parameters of Ketorolac Tromethamine after Intramuscular (IM) and Intranasal (IN) Administration
Ketorolac Tromethamine | Cmax (SD) ng/mL | tmax (range) hours | AUC 0-∞ (SD) ng•h/mL | T½ (SD) hours
30 mg IM (1.0 mL of a 30 mg/mL solution) | 2382.2 (432.7) | 0.75 (0.25-1.03) | 11152.8 (4260.1) | 4.80 (1.18)
31.5 mg IN (SPRIX) (2 x 100 μL of a 15% w/w solution) | 1805.8 (882.8) | 0.75 (0.50-2.00) | 7477.3 (3654.4) | 5.24 (1.33)
15 mg IM (0.5 mL of a 30 mg/mL solution) | 1163.4 (279.9) | 0.75 (0.25-1.50) | 5196.3 (2076.7) | 5.00 (1.72)
Cmax = maximum plasma concentration; tmax = time of Cmax; AUC0-∞ = complete area under the concentration-time curve; T½ = half-life; SD = standard deviation. All values are means, except tmax, for which medians are reported.

Absorption

In a study in which SPRIX (31.5 mg) was administered to healthy volunteers four times daily for 5 days, the Cmax, tmax, and AUC values following the final dose were comparable to those obtained in the single-dose study. Accumulation of ketorolac has not been studied in special populations, geriatric, pediatric, renal failure or hepatic disease patients.

Distribution

Scintigraphic assessment of drug disposition of ketorolac following SPRIX intranasal dosing demonstrated that most of the ketorolac was deposited in the nasal cavity and pharynx, with less than 20% deposited in the esophagus and stomach, and zero or negligible deposition in the lungs (<0.5%).

The mean apparent volume (Vβ) of ketorolac tromethamine following complete distribution was approximately 13 liters. This parameter was determined from single-dose data. The ketorolac tromethamine racemate has been shown to be highly protein bound (99.2%). Nevertheless, plasma concentrations as high as 10 mcg/mL will only occupy approximately 5% of the albumin binding sites. Thus, the unbound fraction for each enantiomer will be constant over the therapeutic range. A decrease in serum albumin, however, will result in increased free drug concentrations. Therapeutic concentrations of digoxin, warfarin, ibuprofen, naproxen, piroxicam, acetaminophen, phenytoin, and tolbutamide did not alter ketorolac protein binding. In vitro studies indicate that, at therapeutic concentrations of salicylate (300 mcg/mL), the binding of ketorolac was reduced from approximately 99.2% to 97.5%, representing a potential twofold increase in unbound ketorolac plasma levels.

The in vitro binding of warfarin to plasma proteins is only slightly reduced by ketorolac (99.5% control vs. 99.3%) when ketorolac plasma concentrations reach 5 to 10 mcg/mL.

Ketorolac tromethamine is excreted in human milk.

Elimination

Metabolism

Ketorolac tromethamine is largely metabolized in the liver. The metabolic products are hydroxylated and conjugated forms of the parent drug. The products of metabolism, and some unchanged drug, are excreted in the urine. There is no evidence in animal or human studies that ketorolac induces or inhibits hepatic enzymes capable of metabolizing itself or other drugs.

Excretion

The principal route of elimination of ketorolac and its metabolites is renal. About 92% of a given dose is found in the urine, approximately 40% as metabolites and 60% as unchanged ketorolac. Approximately 6% of a dose is excreted in the feces. A single-dose study with 10 mg ketorolac tromethamine (n = 9) demonstrated that the S-enantiomer is cleared approximately two times faster than the R-enantiomer and that the clearance was independent of the route of administration. This means that the ratio of S/R plasma concentrations decreases with time after each dose. There is little or no inversion of the R- to S- form in humans.

The half-life of the ketorolac tromethamine S-enantiomer was approximately 2.5 hours (SD ± 0.4) compared with 5 hours (SD ± 1.7) for the R-enantiomer. In other studies, the half-life for the racemate has been reported to lie within the range of 5 to 6 hours.

Specific Populations

Geriatric: A single-dose study was conducted to compare the pharmacokinetics of SPRIX (31.5 mg) in subjects ≥ age 65 to the pharmacokinetics in subjects < age 65. Exposure to ketorolac was increased by 23% for the ≥ 65 population as compared to subjects < 65. Peak concentrations of 2028 and 1840 ng/mL were observed for the elderly and nonelderly adult populations, respectively, at 0.75 h after dosing. In the elderly population a longer terminal half-life was observed as compared to the nonelderly adults (4.5 h vs. 3.3 h, respectively).

Race: Pharmacokinetic differences due to race have not been identified.

Hepatic Impairment: There was no significant difference in estimates of half-life, AUC∞ and Cmax in 7 patients with liver disease compared to healthy volunteers.

Renal Impairment: Based on single-dose data only, the mean half-life of ketorolac tromethamine in renally impaired patients is between 6 and 19 hours, and is dependent on the extent of the impairment. There is poor correlation between creatinine clearance and total ketorolac tromethamine clearance in the elderly and populations with renal impairment (r = 0.5).

In patients with renal disease, the AUC∞ of each enantiomer increased by approximately 100% compared with healthy volunteers. The volume of distribution doubles for the S-enantiomer and increases by 1/5th for the R-enantiomer. The increase in volume of distribution of ketorolac tromethamine implies an increase in unbound fraction. The AUC∞-ratio of the ketorolac tromethamine enantiomers in healthy subjects and patients remained similar, indicating there was no selective excretion of either enantiomer in patients compared to healthy subjects.

Allergic Rhinitis: Comparison of the pharmacokinetics of SPRIX in subjects with allergic rhinitis to data from a previous study in healthy subjects showed no differences that would be of clinical consequence for the efficacy or safety of SPRIX.

Drug Interaction Studies

Aspirin: When NSAIDs were administered with aspirin, the protein binding of NSAIDs were reduced, although the clearance of free NSAID was not altered. The clinical significance of this interaction is not known. See Table 2 for clinically significant drug interactions of NSAIDs with aspirin [see Drug Interactions (7)].

Other Nasal Spray Products: A study was conducted in subjects with symptomatic allergic rhinitis to assess the effects of the commonly used nasal spray products oxymetazoline hydrochloride and fluticasone propionate on the pharmacokinetics of SPRIX. Subjects received a single dose of oxymetazoline nasal spray followed by a single dose (31.5 mg) of SPRIX 30 min later. Subjects also received fluticasone nasal spray (200 mcg as 2 x 50 mcg in each nostril) for seven days, with a single dose (31.5 mg) of SPRIX on the 7th day. Administration of these common intranasal products had no effect of clinical significance on the rate or extent of ketorolac absorption.

Probenecid: Concomitant administration of oral ketorolac and probenecid resulted in decreased clearance and volume of distribution of ketorolac and significant increases in ketorolac plasma levels (total AUC increased approximately threefold from 5.4 to 17.8 mcg/h/mL), and terminal half-life increased approximately twofold from 6.6 to 15.1 hours [see Drug Interactions (7)].

13 NONCLINICAL TOXICOLOGY

13.1 Carcinogenesis, Mutagenesis, Impairment of Fertility

Carcinogenesis

An 18-month study in mice with oral doses of ketorolac at 2 mg/kg/day (approximately 1.3 times the human systemic exposure at the recommended maximum IN dose of 31.5 mg four times a day, based on area-under-the-plasma-concentration curve [AUC]), and a 24-month study in rats at 5 mg/kg/day (approximately 0.8 times the human AUC) showed no evidence of tumorigenicity.

Mutagenesis

Ketorolac was not mutagenic in the Ames test, unscheduled DNA synthesis and repair, or in forward mutation assays. Ketorolac did not cause chromosome breakage in the in vivo mouse micronucleus assay. At 1590 μg/mL and at higher concentrations, ketorolac increased the incidence of chromosomal aberrations in Chinese hamster ovarian cells.

Impairment of fertility

Impairment of fertility did not occur in male or female rats at oral doses of 9 mg/kg (approximately 1.3 times the human AUC) and 16 mg/kg (approximately 2.4 times the human AUC) of ketorolac, respectively.

14 CLINICAL STUDIES

14.1 Postoperative Pain

The effect of SPRIX on acute pain was evaluated in two multi-center, randomized, double-blind, placebo-controlled studies.

In a study of adults who had undergone elective abdominal or orthopedic surgery, 300 patients were randomized and treated with SPRIX or placebo administered every 8 hours and morphine administered via patient controlled analgesia on an as needed basis. Efficacy was demonstrated as a statistically significant greater reduction in the summed pain intensity difference over 48 hours in patients who received SPRIX as compared to those receiving placebo. The clinical relevance of this is reflected in the finding that patients treated with SPRIX required 36% less morphine over 48 hours than patients treated with placebo.

In a study of adults who had undergone elective abdominal surgery, 321 patients were randomized and treated with SPRIX or placebo administered every 6 hours and morphine administered via patient controlled analgesia on an as needed basis. Efficacy was demonstrated as a statistically significant greater reduction in the summed pain intensity difference over 48 hours in patients who received SPRIX as compared to those receiving placebo. The clinical relevance of this is reflected in the finding that patients treated with SPRIX required 26% less morphine over 48 hours than patients treated with placebo.

16 HOW SUPPLIED/STORAGE AND HANDLING

SPRIX (ketorolac tromethamine) Nasal Spray, 15.75 mg/spray, are single-day preservative-free spray bottles, supplied as:

NDC 69344-144-43 Carton containing 5 single-day nasal spray bottles
NDC 69344-144-53 Carton containing 1 single-day nasal spray bottle

Each single-day nasal spray bottle contains a sufficient quantity of solution to deliver 8 sprays for a total of 126 mg of ketorolac tromethamine. Each spray delivers 15.75 mg of ketorolac tromethamine. The delivery system is designed to administer precisely metered doses of 100 µL per spray.

Storage

Protect from light and freezing. Store unopened SPRIX between 2°C to 8°C (36°F to 46°F). During use, keep containers of SPRIX Nasal Spray at controlled room temperature, between 15°C to 30°C (59°F to 86°F), out of direct sunlight. Bottles of SPRIX should be discarded within 24 hours of priming.

17 PATIENT COUNSELING INFORMATION

Advise the patient to read the FDA-approved patient labeling (Medication Guide and Instructions for Use) that accompanies each prescription dispensed. Instruct all patients to read and closely follow the FDA-approved SPRIX Patient Instructions to ensure proper administration of SPRIX. When prescribing SPRIX, inform patients or their caregivers of the potential risks of ketorolac treatment, instruct patients to seek medical advice if they develop treatment-related adverse events, advise patients not to give SPRIX to other family members, and advise patients to discard any unused drug. Inform patients, families, or their caregivers of the following information before initiating therapy with SPRIX and periodically during the course of ongoing therapy.

Cardiovascular Thrombotic Events

Advise patients to be alert for the symptoms of cardiovascular thrombotic events, including chest pain, shortness of breath, weakness, or slurring of speech, and to report any of these symptoms to their health care provider immediately [see Warnings and Precautions (5.1)].

Gastrointestinal Bleeding, Ulceration, and Perforation

Advise patients to report symptoms of ulcerations and bleeding, including epigastric pain, dyspepsia, melena, and hematemesis to their health care provider. In the setting of concomitant use of low-dose aspirin for cardiac prophylaxis, inform patients of the increased risk for and the signs and symptoms of GI bleeding [see Contraindications (4), Warnings and Precautions (5.2)].

Hepatotoxicity

Inform patients of the warning signs and symptoms of hepatotoxicity (e.g., nausea, fatigue, lethargy, pruritus, diarrhea, jaundice, right upper quadrant tenderness, and “flu-like” symptoms). If these occur, instruct patients to stop SPRIX and seek immediate medical therapy [see Warnings and Precautions (5.3)].

Heart Failure and Edema

Advise patients to be alert for the symptoms of congestive heart failure including shortness of breath, unexplained weight gain, or edema and to contact their healthcare provider if such symptoms occur [see Warnings and Precautions (5.5)].

Anaphylactic Reactions

Inform patients of the signs of an anaphylactic reaction (e.g., difficulty breathing, swelling of the face or throat). Instruct patients to seek immediate emergency help if these occur [see Contraindications (4) and Warnings and Precautions (5.7)].

Serious Skin Reactions, including DRESS

Advise patients to stop taking SPRIX immediately if they develop any type of rash or fever and to contact their healthcare provider as soon as possible [see Warnings and Precautions (5.9, 5.10)].

Female Fertility

Advise females of reproductive potential who desire pregnancy that NSAIDs, including SPRIX, may be associated with a reversible delay in ovulation [see Use in Specific Populations (8.3)].

Fetal Toxicity

Inform pregnant women to avoid use of SPRIX and other NSAIDs starting at 30 weeks gestation because of the risk
of the premature closing of the fetal ductus arteriosus. If treatment with SPRIX is needed for a pregnant woman
between about 20 to 30 weeks gestation, advise her that she may need to be monitored for oligohydramnios, if
treatment continues for longer than 48 hours [see Warnings and Precautions (5.10) and Use in Specific Populations (8.1)].

Avoid Concomitant Use of NSAIDs

Inform patients that the concomitant use of SPRIX with other NSAIDs or salicylates (e.g., diflunisal, salsalate) is not recommended due to the increased risk of gastrointestinal toxicity, and little or no increase in efficacy [see Warnings and Precautions (5.2) and Drug Interactions (7)]. Alert patients that NSAIDs may be present in “over the counter” medications for treatment of colds, fever, or insomnia.

Use of NSAIDS and Low-Dose Aspirin

Inform patients not to use low-dose aspirin concomitantly with SPRIX until they talk to their healthcare provider [see Drug Interactions (7)].

Renal Effects

SPRIX is eliminated by the kidneys. Advise patients to maintain adequate fluid intake and request medical advice if urine output decreases significantly [see Contraindications (4), Warnings and Precautions (5.6)].

Limitations of Use

Instruct patients not to use SPRIX for more than 5 days. Use of SPRIX alone or in combination with any other ketorolac product for more than 5 days increases the risk for serious complications including GI bleeding and renal injury [see Dosage and Administration (2)].

Single-Day Container

Instruct patients not to use any single bottle of SPRIX for more than one day [see Dosage and Administration (2.5)].

Nasal Discomfort

Advise patients that they may experience transient, mild to moderate nasal irritation or discomfort upon dosing.

Manufactured for and Distributed by:

Zyla Life Sciences US Inc.
Wayne, PA 19087

LBL # 101.05

Medication Guide for Nonsteroidal Anti-inflammatory Drugs (NSAIDs)

What is the most important information I should know about medicines called Nonsteroidal Anti-inflammatory Drugs (NSAIDs)?
NSAIDs can cause serious side effects, including:

- Increased risk of a heart attack or stroke that can lead to death.This risk may happen early in treatment and may increase:
  - with increasing doses of NSAIDs
  - with longer use of NSAIDs

Do not take NSAIDs right before or after a heart surgery called a “coronary artery bypass graft (CABG)."
Avoid taking NSAIDs after a recent heart attack, unless your healthcare provider tells you to. You may have an increased risk of another heart attack if you take NSAIDs after a recent heart attack.

- Increased risk of bleeding, ulcers, and tears (perforation) of the esophagus (tube leading from the mouth to the stomach), stomach and intestines:
  - anytime during use
  - without warning symptoms
  - that may cause death

The risk of getting an ulcer or bleeding increases with:

- past history of stomach ulcers, or stomach or intestinal bleeding with use of NSAIDs
- taking medicines called “corticosteroids”, “anticoagulants”, “SSRIs”, or “SNRIs”

- increasing doses of NSAIDs
- longer use of NSAIDs
- smoking
- drinking alcohol

- older age
- poor health
- advanced liver disease
- bleeding problems

NSAIDs should only be used:

- exactly as prescribed
- at the lowest dose possible for your treatment
- for the shortest time needed

What are NSAIDs?
NSAIDs are used to treat pain and redness, swelling, and heat (inflammation) from medical conditions such as different types of arthritis, menstrual cramps, and other types of short-term pain.

Who should not take NSAIDs?
Do not take NSAIDs:

- if you have had an asthma attack, hives, or other allergic reaction with aspirin or any other NSAIDs.
- right before or after heart bypass surgery.

Before taking NSAIDs, tell your healthcare provider about all of your medical conditions, including if you:

- have liver or kidney problems
- have high blood pressure
- have asthma
- are pregnant or plan to become pregnant. Taking NSAIDs at about 20 weeks of pregnancy or later may harm
  your unborn baby. If you need to NSAIDs for more than 2 days when you are between 20 and 30 weeks of
  pregnancy, your healthcare provider may need to monitor the amount of fluid in your womb around your
  baby. You should not take NSAIDs after about 30 weeks of pregnancy.
- are breastfeeding or plan to breast feed.

Tell your healthcare provider about all of the medicines you take, including prescription or over-the-counter medicines, vitamins or herbal supplements. NSAIDs and some other medicines can interact with each other and cause serious side effects. Do not start taking any new medicine without talking to your healthcare provider first.

What are the possible side effects of NSAIDs?
NSAIDs can cause serious side effects, including:
See “What is the most important information I should know about medicines called Nonsteroidal Anti-inflammatory Drugs (NSAIDs)?”

- new or worse high blood pressure
- heart failure
- liver problems including liver failure
- kidney problems including kidney failure
- low red blood cells (anemia)
- life-threatening skin reactions
- life-threatening allergic reactions
- Other side effects of NSAIDs include: stomach pain, constipation, diarrhea, gas, heartburn, nausea, vomiting, and dizziness.

Get emergency help right away if you get any of the following symptoms:

- shortness of breath or trouble breathing
- chest pain
- weakness in one part or side of your body

- slurred speech
- swelling of the face or throat

Stop taking your NSAID and call your healthcare provider right away if you get any of the following symptoms:

- nausea
- more tired or weaker than usual
- diarrhea
- itching
- your skin or eyes look yellow
- indigestion or stomach pain
- flu-like symptoms

- vomit blood
- there is blood in your bowel movement or it is black and sticky like tar
- unusual weight gain
- skin rash or blisters with fever
- swelling of the arms, legs, hands and feet

If you take too much of your NSAID, call your healthcare provider or get medical help right away.
These are not all the possible side effects of NSAIDs. For more information, ask your healthcare provider or pharmacist about NSAIDs.
Call your doctor for medical advice about side effects. You may report side effects to FDA at 1-800-FDA-1088.

Other information about NSAIDs

- Aspirin is an NSAID but it does not increase the chance of a heart attack. Aspirin can cause bleeding in the brain, stomach, and intestines. Aspirin can also cause ulcers in the stomach and intestines.
- Some NSAIDs are sold in lower doses without a prescription (over-the-counter). Talk to your healthcare provider before using over-the-counter NSAIDs for more than 10 days.

General information about the safe and effective use of NSAIDs
Medicines are sometimes prescribed for purposes other than those listed in a Medication Guide. Do not use NSAIDs for a condition for which it was not prescribed. Do not give NSAIDs to other people, even if they have the same symptoms that you have. It may harm them.
If you would like more information about NSAIDs, talk with your healthcare provider. You can ask your pharmacist or healthcare provider for information about NSAIDs that is written for health professionals.

Manufactured for: Zyla Life Sciences US Inc., Wayne, PA 19087
Distributed by: Zyla Life Sciences US Inc., Wayne, PA 19087
For more information, go to www.sprix.com or call 1-800-518-1084.

This Medication Guide has been approved by the U.S. Food and Drug Administration.

Issued or Revised: 04/2021

Instructions for Use
SPRIX® (spriks)
(ketorolac tromethamine)
Nasal Spray

Read this Instructions for Use before you start using SPRIX and each time you get a refill. There may be new information. This information does not take the place of talking to your healthcare provider about your medical condition or your treatment.

Important information:

- SPRIX is for use in your nose only. Do not breathe in (inhale) SPRIX.
- Each SPRIX bottle has enough pain medicine for 1 day.
- Throw away each SPRIX bottle within 24 hours of taking your first dose, even if the bottle still contains unused medicine.

Your healthcare provider has prescribed SPRIX to treat moderate to severe pain.

- Use SPRIX exactly as your healthcare provider tells you to use it.
- Your healthcare provider will tell you how many sprays you should use each time you use SPRIX.
- Do not use SPRIX for more than 5 days. If you still have pain after 5 days, contact your healthcare provider.
- Do not use SPRIX more than every 6 hours.
- It is important that you drink plenty of fluids while you are using SPRIX. Tell your healthcare provider if you urinate less while using SPRIX.

You may have discomfort or irritation in your nose when using SPRIX. This usually lasts for a short time. Do not breathe in (inhale) SPRIX while spraying.

Using SPRIX Nasal Spray

Parts of your SPRIX bottle

Follow the instructions below to use SPRIX.

Before you use SPRIX for the first time, you will need to prime the bottle.

Priming SPRIX:

Step 1. Hold the finger flange with your fingers (see Figure A), and remove the clear plastic cover with your opposite hand. Keep the clear plastic cover for later. Remove and throw away the blue plastic safety clip.

If the clear plastic cover is improperly removed, the tip of the bottle may be pulled off of the glass vial. If this happens, place the tip back onto the glass vial by lining it up carefully and gently pushing it back on until it is back in the correct position (see Figure B). The SPRIX bottle should work properly again.

Step 2. Hold the SPRIX bottle upright at arm’s length away from you with your index finger and middle finger resting on the top of the finger flange and your thumb supporting the base (see Figure C).

Press down on the finger flange and release the pump 5 times. You may not see a spray the first few times you press down.

Now the pump is primed and ready to use. You do not need to prime the pump again if you use more doses from this bottle.

Step 3. Blow your nose to clear your nostrils.

Step 4. Sit up straight or stand.

Step 5. Keep your head tilted downward toward your toes.

Step 6. Place the tip of the SPRIX bottle into your right nostril.

Step 7. Hold the SPRIX bottle upright and aim the tip toward the back of your nose (see Figure D).

Step 8. Hold your breath and spray 1 time into your right nostril, pressing down on both sides of the finger flange (see Figure D).

Step 9. Breathe in gently through your mouth after you use SPRIX. You may also pinch your nose to help keep the medicine in your nose.

Step 10. If your healthcare provider has prescribed only 1 spray per dose for you, you have now finished your dose, skip to Step 12 below.

Step 11. If your healthcare provider has prescribed 2 sprays for you, repeat steps 3 - 9 above for your left nostril. Be sure to point the spray away from the center of your nose. Spray 1 time into your left nostril.

Step 12. When you are finished using SPRIX, put the clear plastic cover back on the SPRIX bottle.

How should I store SPRIX?

- Store unopened SPRIX bottles between 36°F to 46°F (2°C to 8°C).
- Keep opened bottles of SPRIX at room temperature.
- Keep SPRIX out of direct sunlight.
- Do not freeze SPRIX.
- SPRIX does not contain a preservative. Throw away each SPRIX bottle within 24 hours of taking your first dose, even if the bottle still contains unused medicine.

Keep SPRIX and all medicines out of the reach of children.

General information about the safe and effective use of SPRIX.

Medicines are sometimes prescribed for purposes other than those listed in a Medication Guide. Do not give SPRIX to other people, even if they have the same symptoms that you have. It may harm them.

You can ask your pharmacist or healthcare provider for information about SPRIX that is written for health professionals.

What are the ingredients in SPRIX?

Active ingredient: ketorolac tromethamine
Inactive ingredient: edetate disodium (EDTA), monobasic potassium phosphate, sodium hydroxide, and water for injection

This Instructions for Use has been approved by the U.S. Food and Drug Administration.

Distributed by:
Zyla Life Sciences US Inc.
Wayne, PA 19087

LBL # 102.04 Revised: 04/2021